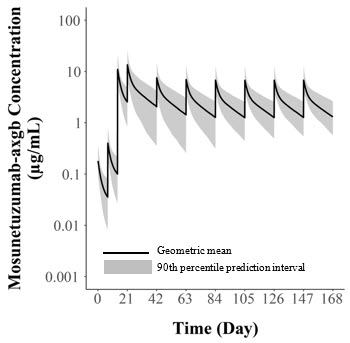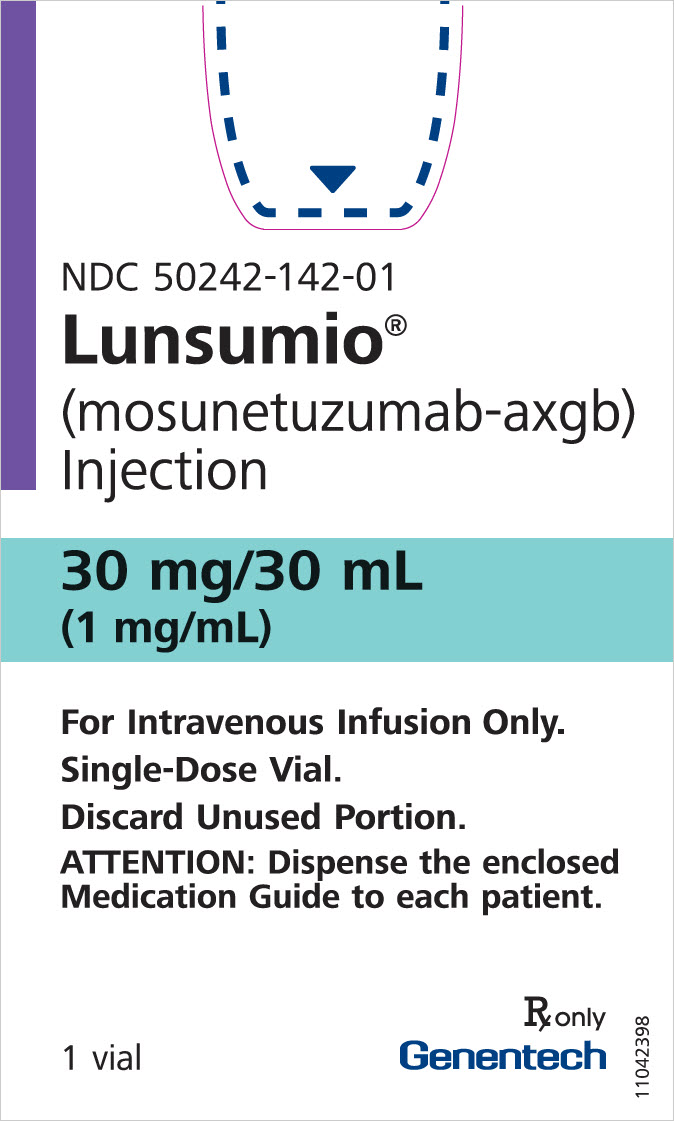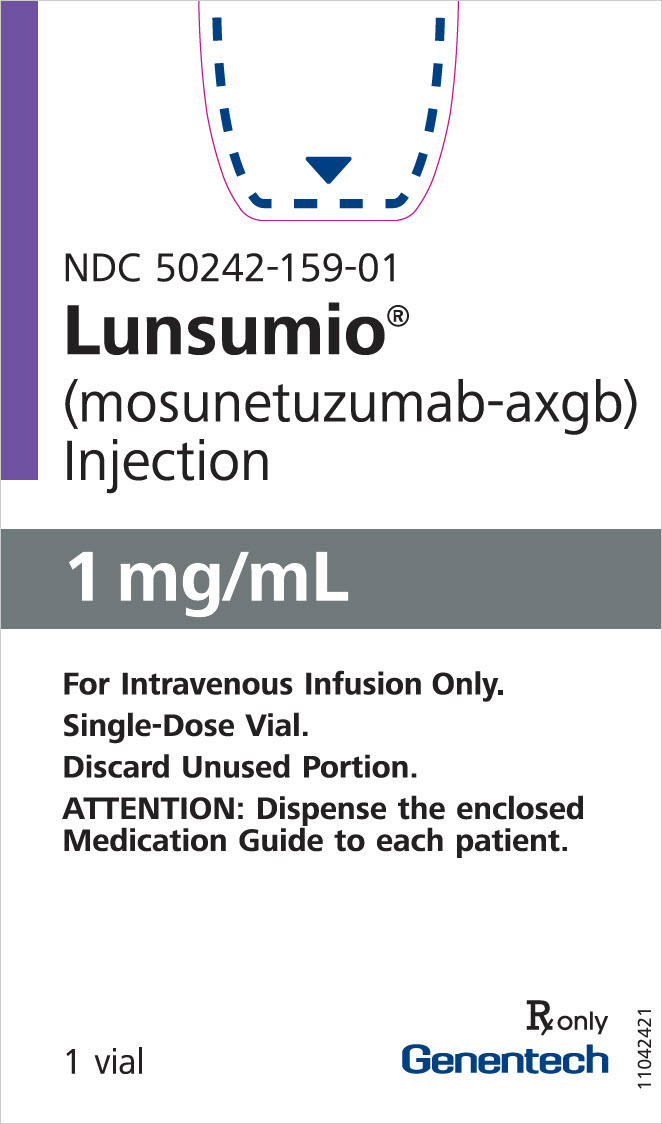 DRUG LABEL: Lunsumio
NDC: 50242-142 | Form: CONCENTRATE
Manufacturer: Genentech, Inc.
Category: prescription | Type: HUMAN PRESCRIPTION DRUG LABEL
Date: 20251208

ACTIVE INGREDIENTS: MOSUNETUZUMAB 30 mg/30 mL
INACTIVE INGREDIENTS: HISTIDINE 46.6 mg/30 mL; ACETIC ACID 12.8 mg/30 mL; METHIONINE 44.8 mg/30 mL; SUCROSE 2462.4 mg/30 mL; POLYSORBATE 20 18 mg/30 mL; WATER

HIGHLIGHTS OF PRESCRIBING INFORMATION

These highlights do not include all the information needed to use LUNSUMIO safely and effectively. See full prescribing information for LUNSUMIO.
LUNSUMIO® (mosunetuzumab-axgb) injection, for intravenous use
Initial U.S. Approval: 2022

WARNING: CYTOKINE RELEASE SYNDROME

See full prescribing information for complete boxed warning.

Cytokine release syndrome (CRS), including serious or life-threatening reactions, can occur in patients receiving LUNSUMIO. Initiate treatment with the LUNSUMIO step-up dosing schedule to reduce the risk of CRS. Withhold LUNSUMIO until CRS resolves or permanently discontinue based on severity. (2.1, 2.4, 5.1)

RECENT MAJOR CHANGES

Dosage and Administration (2.1, 2.3, 2.5) | 12/2025
Warnings and Precautions (5.1, 5.5, 5.7) | 12/2025

1 INDICATIONS AND USAGE

LUNSUMIO is a bispecific CD20-directed CD3 T-cell engager indicated for the treatment of adult patients with relapsed or refractory follicular lymphoma after two or more lines of systemic therapy.

This indication is approved under accelerated approval based on response rate. Continued approval for this indication may be contingent upon verification and description of clinical benefit in a confirmatory trial(s). (1.1)

2 DOSAGE AND ADMINISTRATION

- LUNSUMIO and LUNSUMIO VELO have different dosage and administration instructions. Administer LUNSUMIO only as an intravenous infusion. (2.1)
- Premedicate to reduce risk of CRS and infusion-related reactions. (2.3, 5.1)
- Recommended dosage for LUNSUMIO for intravenous infusion (2.2):

Day of Treatment [Cycle length = 21 days] |  | Intravenous Dose of LUNSUMIO | Rate of Infusion
Cycle 1 | Day 1 | 1 mg | Administer over a minimum of 4 hours.
Cycle 1 | Day 8 | 2 mg | Administer over a minimum of 4 hours.
Cycle 1 | Day 15 | 60 mg | Administer over a minimum of 4 hours.
Cycle 2 | Day 1 | 60 mg | Administer over 2 hours if infusions from Cycle 1 were well-tolerated.
Cycles 3+ | Day 1 | 30 mg | Administer over 2 hours if infusions from Cycle 1 were well-tolerated.

- See Full Prescribing Information for instructions on preparation and administration. (2.5)

3 DOSAGE FORMS AND STRENGTHS

Injection:

- 1 mg/mL solution in a single-dose vial. (3)
- 30 mg/30 mL (1 mg/mL) solution in a single-dose vial. (3)

4 CONTRAINDICATIONS

None. (4)

5 WARNINGS AND PRECAUTIONS

- Neurologic Toxicity, including Immune Effector Cell-Associated Neurotoxicity Syndrome: Can cause serious and life-threatening neurologic toxicity, including immune effector cell-associated neurotoxicity syndrome (ICANS). Monitor patients for signs and symptoms of neurologic toxicity during treatment; withhold or permanently discontinue based on severity. (5.2)
- Infections: Can cause serious or fatal infections. Monitor patients for signs and symptoms of infection, including opportunistic infections, and treat as needed. (5.3)
- Hemophagocytic Lymphohistiocytosis: Can cause serious or fatal reactions. For suspected cases, interrupt LUNSUMIO and evaluate and treat promptly. (5.4)
- Cytopenias: Monitor complete blood cell counts during treatment. (5.5)
- Tumor Flare: Can cause serious tumor flare reactions. Monitor patients at risk for complications of tumor flare. (5.6)
- Risk of Medication Errors with Incorrect Product Use: Ensure that the correct formulation is being prescribed, dispensed, and administered. (5.7)
- Embryo-Fetal Toxicity: May cause fetal harm. Advise females of reproductive potential of the potential risk to the fetus and to use effective contraception. (5.8, 8.1, 8.3)

6 ADVERSE REACTIONS

The most common adverse reactions (≥ 20%) in patients with follicular lymphoma are CRS, fatigue, rash, headache, pyrexia, musculoskeletal pain, cough, pruritus, and peripheral neuropathy.

The most common Grade 3 to 4 laboratory abnormalities (≥ 10%) are decreased lymphocyte count, decreased phosphate, increased glucose, decreased neutrophil count, increased uric acid, decreased hemoglobin, and decreased platelets. (6.1)

To report SUSPECTED ADVERSE REACTIONS, contact Genentech at 1-888-835-2555 or FDA at 1-800-FDA-1088 or www.fda.gov/medwatch.

8 USE IN SPECIFIC POPULATIONS

Lactation: Advise not to breastfeed. (8.2)

FULL PRESCRIBING INFORMATION

WARNING: CYTOKINE RELEASE SYNDROME

Cytokine release syndrome (CRS), including serious or life-threatening reactions, can occur in patients receiving LUNSUMIO. Initiate treatment with the LUNSUMIO step-up dosing schedule to reduce the risk of CRS. Withhold LUNSUMIO until CRS resolves or permanently discontinue based on severity [see Dosage and Administration (2.1 and 2.4) and Warnings and Precautions (5.1)].

1 INDICATIONS AND USAGE

1.1 Follicular Lymphoma

LUNSUMIO is indicated for the treatment of adult patients with relapsed or refractory follicular lymphoma after two or more lines of systemic therapy.

This indication is approved under accelerated approval based on response rate [see Clinical Studies (14)]. Continued approval for this indication may be contingent upon verification and description of clinical benefit in a confirmatory trial(s).

2 DOSAGE AND ADMINISTRATION

2.1 Important Dosing Information

- LUNSUMIO and LUNSUMIO VELO have different dosage and administration instructions [see Dosage and Administration (2.2) and Warnings and Precautions (5.7)].
  - LUNSUMIO is for intravenous use only.
  - Check the product label to ensure that the correct formulation (LUNSUMIO or LUNSUMIO VELO) is being prescribed and administered.
  - Do not substitute LUNSUMIO for or with LUNSUMIO VELO.
- Administer LUNSUMIO to well-hydrated patients.
- Premedicate before each dose in Cycle 1 and Cycle 2 [see Dosage and Administration (2.3)].
- Administer only as an intravenous infusion through a dedicated infusion line. Do not use an in-line filter to administer LUNSUMIO. Drip chamber filters can be used to administer LUNSUMIO.
- LUNSUMIO should only be administered by a qualified healthcare professional with appropriate medical support to manage severe reactions such as CRS and neurologic toxicity, including ICANS [see Warnings and Precautions (5.1 and 5.2)].

2.2 Recommended Dosage

The recommended dosage for LUNSUMIO intravenous infusion is presented in Table 1.

Administer for 8 cycles, unless patients experience unacceptable toxicity or disease progression.

For patients who achieve a complete response, no further treatment beyond 8 cycles is required. For patients who achieve a partial response or have stable disease in response to treatment with LUNSUMIO after 8 cycles, an additional 9 cycles of treatment (17 cycles total) should be administered, unless a patient experiences unacceptable toxicity or disease progression.

Table 1. Recommended Dose and Schedule of LUNSUMIO Intravenous Infusion (21-Day Treatment Cycles)
Day of Treatment |  | Intravenous Dose of LUNSUMIO | Rate of Infusion
Cycle 1 | Day 1 | 1 mg | Administer over a minimum of 4 hours.
Cycle 1 | Day 8 | 2 mg | Administer over a minimum of 4 hours.
Cycle 1 | Day 15 | 60 mg | Administer over a minimum of 4 hours.
Cycle 2 | Day 1 | 60 mg | Administer over 2 hours if infusions from Cycle 1 were well-tolerated.
Cycles 3+ | Day 1 | 30 mg | Administer over 2 hours if infusions from Cycle 1 were well-tolerated.

Table 2. Recommendations for Restarting Therapy with LUNSUMIO Intravenous Infusion After Dose Delay
Last Intravenous Dose Administered | Time Since Last Dose Administered | Action for Next Intravenous Dose(s)
1 mg Cycle 1 Day 1 | 1week to 2 weeks | Administer 2 mg (Cycle 1 Day 8), then resume the planned treatment schedule.
1 mg Cycle 1 Day 1 | Greater than 2 weeks | Repeat 1 mg (Cycle 1 Day 1), then administer 2 mg (Cycle 1 Day 8) and resume the planned treatment schedule.
2 mg Cycle 1 Day 8 | 1 week to 2 weeks | Administer 60 mg (Cycle 1 Day 15), then resume the planned treatment schedule.
2 mg Cycle 1 Day 8 | Greater than 2 weeks to less than 6 weeks | Repeat 2 mg (Cycle 1 Day 8), then administer 60 mg (Cycle 1 Day 15) and resume the planned treatment schedule.
2 mg Cycle 1 Day 8 | Greater than or equal to 6 weeks | Repeat 1 mg (Cycle 1 Day 1) and 2 mg (Cycle 1 Day 8), then administer 60 mg (Cycle 1 Day 15) and resume the planned treatment schedule.
60 mg Cycle 1 Day 15 | 1 week to less than 6 weeks | Administer 60 mg (Cycle 2 Day 1), then resume the planned treatment schedule.
60 mg Cycle 1 Day 15 | Greater than or equal to 6 weeks | Repeat 1 mg (Cycle 2 Day 1) and 2 mg (Cycle 2 Day 8), then administer 60 mg (Cycle 2 Day 15), followed by 30 mg (Cycle 3 Day 1) and then resume the planned treatment schedule.
60 mg Cycle 2 Day 1 | 3 weeks to less than 6 weeks | Administer 30 mg (Cycle 3 Day 1), then resume the planned treatment schedule.
60 mg Cycle 2 Day 1 | Greater than or equal to 6 weeks | Repeat 1 mg (Cycle 3 Day 1) and 2 mg (Cycle 3 Day 8), then administer 30 mg (Cycle 3 Day 15) [For the Day 1, Day 8, and Day 15 doses in the next cycle, administer premedication as per Table 3 for all patients.] , followed by 30 mg (Cycle 4 Day 1) and then resume the planned treatment schedule.
30 mg Cycle 3 onwards | 3 weeks to less than 6 weeks | Administer 30 mg, then resume the planned treatment schedule.
30 mg Cycle 3 onwards | Greater than or equal to 6 weeks | Repeat 1 mg on Day 1 and 2 mg on Day 8 during the next cycle, then administer 30 mg on Day 15, followed by 30 mg on Day 1 of subsequent cycles.

2.3 Recommended Premedication

Premedication to reduce the risk of CRS and infusion-related reactions are outlined in Table 3 [see Warnings and Precautions (5.1)].

Table 3. Premedication to be Administered to Patients Prior to LUNSUMIO Intravenous Infusion
Treatment Cycle | Patients Requiring Premedication | Premedication | Dosage | Administration
Cycle 1 and Cycle 2 | All patients | Corticosteroid | Dexamethasone 20 mg (preferred) intravenous or methylprednisolone 80 mg intravenous | Complete at least 1 hour prior to infusion
Cycle 1 and Cycle 2 | All patients | Antihistamine | Diphenhydramine hydrochloride 50 mg to 100 mg or equivalent oral or intravenous antihistamine | At least 30 minutes prior to infusion
Cycle 1 and Cycle 2 | All patients | Antipyretic | Oral acetaminophen (500 mg to 1,000 mg) | At least 30 minutes prior to infusion
Cycles 3+ | Patients who experienced any grade CRS with the previous dose | Corticosteroid | Dexamethasone 20 mg (preferred) intravenous or methylprednisolone 80 mg intravenous | Complete at least 1 hour prior to infusion
Cycles 3+ | Patients who experienced any grade CRS with the previous dose | Antihistamine | Diphenhydramine hydrochloride 50 mg to 100 mg or equivalent oral or intravenous antihistamine | At least 30 minutes prior to infusion
Cycles 3+ | Patients who experienced any grade CRS with the previous dose | Antipyretic | Oral acetaminophen (500 mg to 1,000 mg) | At least 30 minutes prior to infusion

2.4 Dosage Modifications for Adverse Reactions

See Tables 4 and 5 for the recommended dosage modifications for adverse reactions of CRS and neurologic toxicity, including immune effector cell-associated neurotoxicity (ICANS). See Table 6 for the recommended dosage modifications for other adverse reactions following administration of LUNSUMIO.

Dosage Modifications for Cytokine Release Syndrome

Identify CRS based on clinical presentation [see Warnings and Precautions (5.1)]. Evaluate for and treat other causes of fever, hypoxia, and hypotension.

If CRS is suspected, withhold LUNSUMIO until CRS resolves, manage according to the recommendations in Table 4 and per current practice guidelines. Administer supportive therapy for CRS, which may include intensive care for severe or life-threatening CRS.

Table 4. Recommendations for Management of Cytokine Release Syndrome with LUNSUMIO Intravenous Infusion
Grade [Based on American Society for Transplantation and Cellular Therapy (ASTCT) 2019 grading for CRS.] | Presenting Symptoms | Actions [If CRS is refractory to management, consider other causes including hemophagocytic lymphohistiocytosis [see Warnings and Precautions (5.4)].]
Grade 1 | Fever ≥ 100.4°F (38°C) [Premedication may mask fever, therefore if clinical presentation is consistent with CRS, follow these management guidelines.] | - Withhold current infusion of LUNSUMIO and manage per current practice guidelines. - If symptoms resolve, restart infusion at the same rate. - Ensure CRS symptoms are resolved for at least 72 hours prior to the next dose of LUNSUMIO. [Refer to Table 2 for information on restarting LUNSUMIO after dose delays [see Dosage and Administration (2.2)].] - Administer premedication [Refer to Table 3 for additional information on premedication.] prior to next dose of LUNSUMIO and monitor patient more frequently.
Grade 2 | Fever ≥ 100.4°F (38°C) with: Hypotension not requiring vasopressors and/or hypoxia requiring low-flow oxygen [Low-flow oxygen defined as oxygen delivered at < 6 L/minute; high-flow oxygen defined as oxygen delivered at ≥ 6 L/minute.] by nasal cannula or blow-by. | - Withhold current infusion of LUNSUMIO and manage per current practice guidelines. - If symptoms resolve, restart infusion at 50% rate. - Ensure CRS symptoms are resolved for at least 72 hours prior to the next dose of LUNSUMIO. - Administer premedication prior to next dose of LUNSUMIO and consider infusing the next dose at 50% rate. - For the next dose of LUNSUMIO, monitor more frequently and consider hospitalization.
Grade 2 | Fever ≥ 100.4°F (38°C) with: Hypotension not requiring vasopressors and/or hypoxia requiring low-flow oxygen [Low-flow oxygen defined as oxygen delivered at < 6 L/minute; high-flow oxygen defined as oxygen delivered at ≥ 6 L/minute.] by nasal cannula or blow-by. | Recurrent Grade 2 CRS; - Manage per Grade 3 CRS.
Grade 3 | Fever ≥ 100.4°F (38°C) with: Hypotension requiring a vasopressor (with or without vasopressin) and/or hypoxia requiring high flow oxygen by nasal cannula, face mask, non-rebreather mask, or Venturi mask. | - Withhold LUNSUMIO, manage per current practice guidelines and provide supportive therapy, which may include intensive care. - Ensure CRS symptoms are resolved for at least 72 hours prior to the next dose of LUNSUMIO. - Administer premedication prior to next dose of LUNSUMIO and infuse the next dose at 50% rate. - Hospitalize for the next dose of LUNSUMIO.
Grade 3 | Fever ≥ 100.4°F (38°C) with: Hypotension requiring a vasopressor (with or without vasopressin) and/or hypoxia requiring high flow oxygen by nasal cannula, face mask, non-rebreather mask, or Venturi mask. | Recurrent Grade 3 CRS; - Permanently discontinue LUNSUMIO. - Manage CRS per current practice guidelines and provide supportive therapy, which may include intensive care.
Grade 4 | Fever ≥ 100.4°F (38°C) with: Hypotension requiring multiple vasopressors (excluding vasopressin) and/or hypoxia requiring oxygen by positive pressure (e.g., CPAP, BiPAP, intubation and mechanical ventilation). | - Permanently discontinue LUNSUMIO. - Manage CRS per current practice guidelines and provide supportive therapy, which may include intensive care.

Dosage Modifications for Neurologic Toxicity, including ICANS

Management recommendations for neurologic toxicity, including ICANS, are summarized in Table 5. At the first sign of neurologic toxicity, including ICANS, consider neurology evaluation and withholding of LUNSUMIO based on the type and severity of neurotoxicity. Rule out other causes of neurologic symptoms. Provide supportive therapy, which may include intensive care.

Table 5. Recommendations for Management of Neurologic Toxicity (including ICANS)
Adverse Reaction | Severity [Based on National Cancer Institute Common Terminology Criteria for Adverse Events (NCI CTCAE), version 4.0.] , [Based on American Society for Transplantation and Cellular Therapy (ASTCT) 2019 grading for ICANS.] | Actions
Neurologic Toxicity (including ICANS) | Grade 1 | - Continue LUNSUMIO and monitor neurologic toxicity symptoms. - If ICANS, manage per current practice guidelines.
Neurologic Toxicity (including ICANS) | Grade 2 | - Withhold LUNSUMIO until neurologic toxicity symptoms improve to Grade 1 or baseline for at least 72 hours. [See Table 2 for recommendations on restarting LUNSUMIO after dose delays [see Dosage and Administration (2.2)].] - Provide supportive therapy, and consider neurologic evaluation. - If ICANS, manage per current practice guidelines.
Neurologic Toxicity (including ICANS) | Grade 3 | - Withhold LUNSUMIO until neurologic toxicity symptoms improve to Grade 1 or baseline for at least 72 hours. - Provide supportive therapy, which may include intensive care, and consider neurology evaluation. - If ICANS, manage per current practice guidelines. - If recurrence of ICANS, permanently discontinue LUNSUMIO.
Neurologic Toxicity (including ICANS) | Grade 4 | - Permanently discontinue LUNSUMIO. - Provide supportive therapy, which may include intensive care, and consider neurology evaluation. - If ICANS, manage per current practice guidelines.

Other Adverse Reactions

Table 6. Recommended Dosage Modification for Other Adverse Reactions
Adverse Reactions [Based on National Cancer Institute Common Terminology Criteria for Adverse Events (NCI CTCAE), version 4.0.] | Severity | Actions
Infections [see Warnings and Precautions (5.3)] | Grades 1 – 4 | - Withhold LUNSUMIO in patients with active infection until the infection resolves. [See Table 2 for recommendations on restarting LUNSUMIO after dose delays [see Dosage and Administration (2.2)].] - For Grade 4, consider permanent discontinuation of LUNSUMIO.
Neutropenia [see Warnings and Precautions (5.4)] | Absolute neutrophil count less than 0.5 × 10^9/L | - Withhold LUNSUMIO until absolute neutrophil count is 0.5 × 10^9/L or higher.
Other Adverse Reactions [see Warnings and Precautions (5.5) and Adverse Reactions (6.1)] | Grade 3 or higher | - Withhold LUNSUMIO until the toxicity resolves to Grade 1 or baseline.

2.5 Preparation and Administration

To prevent medication errors, check the vial labels to ensure that the drug being prepared and administered is LUNSUMIO for intravenous infusion. A peel-off label is provided on the LUNSUMIO Prescribing Information that should be attached to the final prepared solution. Remove the peel-off label from the Prescribing Information in the LUNSUMIO carton before discarding the carton. Affix the peel-off label to the diluted LUNSUMIO infusion bag.

Preparation

Use aseptic technique to prepare LUNSUMIO.

- Inspect the vial visually for any particulate matter, prior to administration. Do not use if the solution is discolored, or cloudy, or if foreign particles are present.
- Determine the dose, the total volume of LUNSUMIO solution required, and the number of LUNSUMIO vials needed.

Dilution

1. Withdraw the volume from an infusion bag of 0.9% Sodium Chloride Injection, USP or 0.45% Sodium Chloride Injection, USP equal to the volume of the LUNSUMIO required for the patient's dose and discard. Only use infusion bags made of polyvinyl chloride (PVC) or polyolefin (PO) such as polyethylene (PE) and polypropylene (PP).
2. Withdraw the required volume of LUNSUMIO from the vial using a sterile needle and syringe and dilute into the infusion bag of 0.9% Sodium Chloride Injection, USP or 0.45% Sodium Chloride Injection, USP according to Table 7. Discard any unused portion left in the vial.

Table 7. Dilution of LUNSUMIO
Dose of LUNSUMIO | Volume of LUNSUMIO | Size of 0.9% or 0.45% Sodium Chloride Injection Infusion Bag
1 mg | 1 mL | 50 mL or 100 mL
2 mg | 2 mL | 50 mL or 100 mL
60 mg | 60 mL | 100 mL or 250 mL
30 mg | 30 mL | 50 mL, 100 mL, or 250 mL

3. Gently mix the intravenous bag by slowly inverting the bag. Do not shake.
4. Parenteral drug products should be inspected visually for particulate matter and discoloration prior to administration, whenever solution and container permit. Do not use if visibly opaque particles, discoloration, or foreign particles are observed.
5. Apply the peel-off label from the Prescribing Information to the infusion bag.
6. Immediately use diluted LUNSUMIO infusion solution. If not used immediately, the diluted solution can be stored refrigerated at 2°C to 8°C (36°F to 46°F) for up to 24 hours and at ambient temperature 9°C to 30°C (48°F to 86°F) for up to 16 hours. Prior to administration, ensure the infusion solution comes to reach room temperature.

Administration

- Administer LUNSUMIO as an intravenous infusion only.
- Do not use an in-line filter to administer LUNSUMIO.
- Do not mix LUNSUMIO with, or administer through the same infusion line, as other medicinal products.
- No incompatibilities have been observed with infusion sets or infusion aids with product contacting materials of PVC, PE, polyurethane (PUR), polybutadiene (PBD), silicone, acrylonitrile butadiene styrene (ABS), polycarbonate (PC), polyetherurethane (PEU), fluorinated ethylene propylene (FEP), or polytetrafluorethylene (PTFE), or with drip chamber filter membrane composed of polyamide (PA).

3 DOSAGE FORMS AND STRENGTHS

LUNSUMIO is a sterile, colorless solution for intravenous infusion available as:

- Injection: 1 mg/mL in a single-dose vial
- Injection: 30 mg/30 mL (1 mg/mL) in a single-dose vial

4 CONTRAINDICATIONS

None.

5 WARNINGS AND PRECAUTIONS

5.1 Cytokine Release Syndrome

LUNSUMIO can cause CRS, including serious or life-threatening reactions [see Adverse Reactions (6.1)].

CRS occurred in 39% of patients who received LUNSUMIO at the recommended dosage in the clinical trial, with Grade 1 CRS occurring in 28%, Grade 2 in 15%, Grade 3 in 2%, and Grade 4 in 0.5% of patients. Among 86 patients who experienced CRS, CRS recurred in 28%. Most cases of CRS occurred following doses of 1 mg on Cycle 1 Day 1 (15%), 2 mg on Cycle 1 Day 8 (5%), and 60 mg on Cycle 1 Day 15 (33%). Five percent of patients experienced CRS after receiving 60 mg on Cycle 2 Day 1 with 1% of patients experiencing CRS following subsequent dosages of LUNSUMIO.

The median time to onset of CRS from the start of administration of LUNSUMIO in Cycle 1 Day 1 was 5 hours (range: 1 hour to 3 days), Cycle 1 Day 8 was 28 hours (range: 5 hours to 3 days), Cycle 1 Day 15 was 25 hours (range: 0.1 hours to 16 days), and Cycle 2 Day 1 was 46 hours (range: 12 hours to 3 days). The median duration of CRS was 3 days (range: 1 to 29 days).

Clinical signs and symptoms of CRS included, but were not limited to, fever, chills, hypotension, tachycardia, hypoxia, and headache. Concurrent neurologic adverse reactions occurred in 6% of patients and included but were not limited to headache, confusional state, and anxiety.

Initiate therapy according to LUNSUMIO step-up dosing schedule to reduce the risk of CRS [see Dosage and Administration (2.3)]. Administer pretreatment medications to reduce the risk of CRS, ensure adequate hydration, and monitor patients following administration of LUNSUMIO accordingly.

At the first sign of CRS, immediately evaluate patients for hospitalization, manage per current practice guidelines and administer supportive care; withhold or permanently discontinue LUNSUMIO based on severity [see Dosage and Administration (2.4)].

Patients who experience CRS (or other adverse reactions that impair consciousness) should be evaluated and advised not to drive and to refrain from operating heavy or potentially dangerous machinery until resolution.

5.2 Neurologic Toxicity, including Immune Effector Cell-Associated Neurotoxicity Syndrome

LUNSUMIO can cause serious and life-threatening neurologic toxicity, including immune effector cell-associated neurotoxicity syndrome (ICANS) [see Adverse Reactions (6.1)].

Neurologic toxicity occurred in 39% of patients who received LUNSUMIO at the recommended dosage in the clinical trial, with Grade 3 neurologic toxicity occurring in 3% of patients. The most frequent neurologic toxicities were headache (21%), peripheral neuropathy (13%), dizziness (11%) and mental status changes (6%, including confusional state, disturbance in attention, cognitive disorder, delirium, encephalopathy, and somnolence). ICANS was reported in 1% of patients (Grade 1: 0.5%, Grade 2: 0.5%) who received LUNSUMIO at the recommended dosage in the clinical trial.

Across a broader clinical trial population, ICANS or suspected ICANS occurred in 2.2% (21/949) of patients who received LUNSUMIO or LUNSUMIO VELO. The most frequent manifestations included confusional state and lethargy. Twenty patients had Grade 1-2 events and 1 patient had a Grade 3 event. The majority of cases (75%) occurred during the first cycle of treatment. The median time to onset was 17 days (range: 1 to 48 days). In total, 88% of cases resolved after a median duration of 3 days (range: 1 to 20 days).

Coadministration of LUNSUMIO with other products that cause dizziness or mental status changes may increase the risk of neurologic toxicity.

Monitor patients for signs and symptoms of neurologic toxicity during treatment. At the first sign of neurologic toxicity, including ICANS, immediately evaluate the patient, consider neurology evaluation as appropriate, and provide supportive therapy based on severity; withhold or permanently discontinue LUNSUMIO based on severity and follow management recommendations [see Dosage and Administration (2.4)].

Patients who experience neurologic toxicity such as tremors, dizziness, insomnia, severe neurotoxicity, or any other adverse reactions that impair consciousness should be evaluated, including potential neurology evaluation, and patients at increased risk should be advised not to drive and to refrain from operating heavy or potentially dangerous machinery until resolution.

5.3 Infections

LUNSUMIO can cause serious or fatal infections [see Adverse Reactions (6.1)].

Among patients who received LUNSUMIO at the recommended dosage in the clinical trial, serious infections, including opportunistic infections, occurred in 17%, with Grade 3 or 4 infections in 14% and fatal infections in 0.9% of patients. The most common Grade 3 or greater infections were pneumonia, sepsis, and upper respiratory infection.

Monitor patients for signs and symptoms of infection prior to and during treatment with LUNSUMIO and treat appropriately. LUNSUMIO should not be administered in the presence of active infection. Caution should be exercised when considering the use of LUNSUMIO in patients with a history of recurring or chronic infections (e.g., chronic, active Epstein-Barr Virus), with underlying conditions that may predispose to infections or who have had significant prior immunosuppressive treatment. Administer prophylactic antimicrobials according to guidelines.

Withhold LUNSUMIO or consider permanent discontinuation of LUNSUMIO based on severity [see Dosage and Administration (2.4)].

5.4 Hemophagocytic Lymphohistiocytosis

LUNSUMIO can cause fatal or serious hemophagocytic lymphohistiocytosis (HLH). HLH is a potentially life-threatening, hyperinflammatory syndrome that is independent of CRS. Common manifestations include fever, elevated ferritin, hemophagocytosis, cytopenias, coagulopathy, hepatitis, and splenomegaly.

Across a broader clinical trial population, HLH occurred in 0.5% (7/1536) of patients. Most cases (5/7) were identified within the first 28 days following initiation of LUNSUMIO or LUNSUMIO VELO, with 3 cases preceded by diagnosed or suspected CRS. Of the 7 cases of HLH, 6 had fatal outcomes, with 2 deaths from HLH alone and 4 deaths with concurrent unresolved HLH. Of the 7 cases of HLH, 4 occurred in the context of concurrent EBV and/or CMV infection.

Monitor for clinical signs and symptoms of HLH. Consider HLH when the presentation of CRS is atypical or prolonged, or when there are features of macrophage activation. For suspected HLH, interrupt LUNSUMIO and evaluate and treat promptly for HLH per current practice guidelines.

5.5 Cytopenias

LUNSUMIO can cause serious or severe cytopenias, including lymphopenia, neutropenia, anemia, and thrombocytopenia [see Adverse Reactions (6.1)].

Among patients who received LUNSUMIO at the recommended dosage in the clinical trial, Grade 3 or 4 decreased lymphocytes occurred in 92%, decreased neutrophils in 38%, decreased hemoglobin in 19%, and decreased platelets in 12% of patients. Grade 4 decreased lymphocytes occurred in 71%, decreased neutrophils in 19%, and decreased platelets in 5% of patients. Febrile neutropenia occurred in 2% of patients.

Monitor complete blood counts throughout treatment. Based on the severity of cytopenias, temporarily withhold, or permanently discontinue LUNSUMIO. Consider prophylactic granulocyte colony-stimulating factor administration as applicable [see Dosage and Administration (2.4)].

5.6 Tumor Flare

LUNSUMIO can cause serious or severe tumor flare [see Adverse Reactions (6.1)].

Among patients who received LUNSUMIO at the recommended dosage in the clinical trial, tumor flare occurred in 4%. Manifestations included new or worsening pleural effusions, localized pain and swelling at the sites of lymphoma lesions, and tumor inflammation.

Patients with bulky tumors or disease located in close proximity to airways or a vital organ should be monitored closely during initial therapy. Monitor for signs and symptoms of compression or obstruction due to mass effect secondary to tumor flare. If compression or obstruction develops, institute standard treatment of these complications.

5.7 Risk of Medication Errors with Incorrect Product Use

Mosunetuzumab-axgb is available in two formulations: as an injection for intravenous use (LUNSUMIO) and as an injection for subcutaneous use (LUNSUMIO VELO). Check the product labels to ensure that the correct formulation is being prescribed, dispensed, and administered to the patient [see Dosage and Administration (2.2 and 2.5)]. Do not substitute LUNSUMIO for or with LUNSUMIO VELO.

5.8 Embryo-Fetal Toxicity

Based on its mechanism of action, LUNSUMIO may cause fetal harm when administered to a pregnant woman. Advise pregnant women of the potential risk to the fetus. Advise females of reproductive potential to use effective contraception during treatment with LUNSUMIO and for 3 months after the last dose [see Use in Specific Populations (8.1, 8.3)].

6 ADVERSE REACTIONS

The following adverse reactions are described elsewhere in the labeling:

- Cytokine Release Syndrome [see Warnings and Precautions (5.1)]
- Neurologic Toxicity, including Immune Effector Cell-associated Neurotoxicity Syndrome [see Warnings and Precautions (5.2)]
- Infections [see Warnings and Precautions (5.3)]
- Hemophagocytic Lymphohistiocytosis [see Warnings and Precautions (5.4)]
- Cytopenias [see Warnings and Precautions (5.5)]
- Tumor Flare [see Warnings and Precautions (5.6)]

6.1 Clinical Trials Experience

Because clinical trials are conducted under widely varying conditions, adverse reaction rates observed in the clinical trials of a drug cannot be directly compared to rates in the clinical trials of another drug and may not reflect the rates observed in practice.

The pooled safety population described in the WARNINGS AND PRECAUTIONS reflects exposure to LUNSUMIO as a single agent in GO29781 in 218 patients with hematologic malignancies in an open-label, multicenter, multi-cohort study. Patients received step-up doses of 1 mg on Cycle 1 Day 1 and 2 mg on Cycle 1 Day 8, followed by 60 mg on Cycle 1 Day 15, and 60 mg on Cycle 2 Day 1, then 30 mg every 3 weeks in subsequent cycles. Each treatment cycle was 21 days. Among 218 patients who received LUNSUMIO, 52% were exposed for at least 8 cycles and 8% were exposed for 17 cycles.

In this pooled safety population, the most common (≥ 20%) adverse reactions were CRS (39%), fatigue (36%), rash (34%), pyrexia (24%), and headache (21%). The most common Grade 3 to 4 laboratory abnormalities (≥ 10%) were decreased lymphocyte count (92%), decreased phosphate (41%), increased glucose (40%), decreased neutrophil count (38%), decreased hemoglobin (19%), increased uric acid (15%), and decreased platelets (12%).

Relapsed or Refractory Follicular Lymphoma

The safety of LUNSUMIO was evaluated in GO29781, an open-label, multicenter, multi-cohort study which included a cohort of 90 patients with relapsed or refractory follicular lymphoma (FL) [see Clinical Studies (14)]. In this cohort, patients with relapsed or refractory FL were required to have received at least two prior lines of systemic therapy, including an anti-CD20 monoclonal antibody and an alkylating agent. Patients received step-up doses of 1 mg on Cycle 1 Day 1 and 2 mg on Cycle 1 Day 8, followed by 60 mg on Cycle 1 Day 15 and 60 mg on Cycle 2 Day 1, then 30 mg every 3 weeks in subsequent cycles. A treatment cycle was 21 days. The median number of cycles was 8 (range: 1 to 17). In the relapsed or refractory FL cohort, 77% were exposed for at least 8 cycles and 12% were exposed for 17 cycles.

The median age was 60 years (range: 29 to 90 years), 61% were male, 82% were White, 4% were Black or African American, 9% were Asian, and 8% were Hispanic or Latino.

Serious adverse reactions occurred in 47% of patients who received LUNSUMIO. Serious adverse reactions in ≥ 2% of patients included CRS, infection (including sepsis, pneumonia, urinary tract infection, EBV viremia, COVID-19, and upper respiratory tract infection), renal insufficiency, pyrexia, and tumor flare.

Permanent discontinuation of LUNSUMIO due to an adverse reaction occurred in 3% of patients. Adverse reactions resulting in permanent discontinuation of LUNSUMIO included CRS and EBV viremia.

Dosage interruptions of LUNSUMIO due to an adverse reaction occurred in 37% of patients. Adverse reactions which required dosage interruption in ≥ 5% of patients included neutropenia, infection, and CRS.

Table 8 summarizes the adverse reactions in patients with relapsed or refractory FL treated with LUNSUMIO in GO29781.

Table 8. Adverse Reactions (≥ 10%) in Patients with Relapsed or Refractory FL Who Received LUNSUMIO Intravenous Infusion in GO29781
Adverse Reaction [Adverse reactions were graded based on CTCAE Version 4.0, with the exception of CRS, which was graded per ASTCT 2019 criteria.] | LUNSUMIO (N = 90)
Adverse Reaction [Adverse reactions were graded based on CTCAE Version 4.0, with the exception of CRS, which was graded per ASTCT 2019 criteria.] | All Grades (%) | Grade 3 or 4 (%)
Immune system disorders
Cytokine release syndrome | 44 | 2.2
General disorders and administration site conditions
Fatigue [Fatigue includes fatigue, asthenia, and lethargy.] | 42 | 0
Pyrexia | 29 | 1.1 [Only Grade 3 adverse reactions occurred.]
Edema [Edema includes edema, edema peripheral, peripheral swelling, face edema, swelling face, pulmonary edema, fluid overload, and fluid retention.] | 17 | 1.1
Chills | 13 | 1.1
Skin and subcutaneous tissue disorders
Rash [Rash includes rash, rash erythematous, exfoliative rash, rash macular, rash maculo-papular, rash papular, rash pruritic, rash pustular, erythema, palmar erythema, dermatitis, and dermatitis acneiform.] | 39 | 4.4
Pruritus | 21 | 0
Dry skin | 16 | 0
Skin exfoliation | 10 | 0
Nervous system
Headache [Headache includes headache and migraine.] | 32 | 1.1
Peripheral neuropathy [Peripheral neuropathy includes peripheral neuropathy, peripheral sensory neuropathy, paresthesia, dysesthesia, hypoesthesia, burning sensation, and neuralgia.] | 20 | 0
Dizziness [Dizziness includes dizziness and vertigo.] | 12 | 0
Musculoskeletal and connective tissue disorders
Musculoskeletal pain [Musculoskeletal pain includes musculoskeletal pain, back pain, myalgia, musculoskeletal chest pain, and neck pain.] | 28 | 1.1
Arthralgia | 11 | 0
Respiratory, thoracic, and mediastinal disorders
Cough [Cough includes cough, productive cough, and upper airway cough syndrome.] | 22 | 0
Dyspnea [Dyspnea includes dyspnea and dyspnea exertional.] | 11 | 1.1
Gastrointestinal disorders
Diarrhea | 17 | 0
Nausea | 17 | 0
Abdominal pain [Abdominal pain includes abdominal pain, lower abdominal pain, and abdominal discomfort.] | 12 | 1.1
Infections
Upper respiratory tract infection [Upper respiratory tract infection includes upper respiratory tract infection, nasopharyngitis, sinusitis, and rhinovirus infection.] | 14 | 2.2
Urinary tract infection [Urinary tract infection includes urinary tract infection and acute pyelonephritis.] | 10 | 1.1
Psychiatric disorder
Insomnia | 12 | 0

Clinically relevant adverse reactions in < 10% of patients who received LUNSUMIO included pneumonia, sepsis, COVID-19, EBV viremia, mental status changes, tumor lysis syndrome, renal insufficiency, anxiety, motor dysfunction (including ataxia, gait disturbance and tremor), tumor flare, and ICANS.

Table 9 summarizes the laboratory abnormalities in patients with relapsed or refractory FL treated with LUNSUMIO in GO29781.

Table 9. Select Laboratory Abnormalities (≥ 20%) That Worsened from Baseline in Patients with Relapsed or Refractory FL Who Received LUNSUMIO Intravenous Infusion in GO29781
Laboratory Abnormality | LUNSUMIO [The denominator used to calculate the rate varied from 72 to 90 based on the number of patients with a baseline value and at least one post-treatment value.]
Laboratory Abnormality | All Grades (%) | Grade 3 or 4 (%)
Hematology
Lymphocyte count decreased | 100 | 98
Hemoglobin decreased | 68 | 12
Neutrophils decreased | 58 | 40
Platelets decreased | 46 | 10
Chemistry
Phosphate decreased | 78 | 46
Glucose increased | 42 | 42
Aspartate aminotransferase increased | 39 | 4.4
Gamma-glutamyl transferase increased | 34 | 9
Magnesium decreased | 34 | 0
Potassium decreased | 33 | 6
Alanine aminotransferase increased | 32 | 7
Uric acid increased | 22 | 22

7 DRUG INTERACTIONS

Effect of LUNSUMIO on CYP450 Substrates

LUNSUMIO causes release of cytokines [see Clinical Pharmacology (12.2)] that may suppress activity of CYP450 enzymes, resulting in increased exposure of CYP450 substrates. Increased exposure of CYP450 substrates is more likely to occur after the first dose of LUNSUMIO on Cycle 1 Day 1 and up to 14 days after the 60 mg dose on Cycle 2 Day 1 and during and after CRS [see Warnings and Precautions (5.1)]. Monitor for toxicity or concentrations of drugs that are CYP450 substrates where minimal concentration changes may lead to serious adverse reactions. Consult the concomitant CYP450 substrate drug prescribing information for recommended dosage modification.

8 USE IN SPECIFIC POPULATIONS

8.1 Pregnancy

Risk Summary

Based on the mechanism of action, LUNSUMIO may cause fetal harm when administered to a pregnant woman [see Clinical Pharmacology (12.1)]. There are no available data on the use of LUNSUMIO in pregnant women to evaluate for a drug-associated risk. No animal reproductive or developmental toxicity studies have been conducted with mosunetuzumab-axgb.

Mosunetuzumab-axgb causes T-cell activation and cytokine release; immune activation may compromise pregnancy maintenance. In addition, based on expression of CD20 on B-cells and the finding of B-cell depletion in non-pregnant animals, mosunetuzumab-axgb can cause B-cell lymphocytopenia in infants exposed to mosunetuzumab-axgb in-utero. Human immunoglobulin G (IgG) is known to cross the placenta; therefore, LUNSUMIO has the potential to be transmitted from the mother to the developing fetus. Advise women of the potential risk to the fetus.

In the U.S. general population, the estimated background risk of major birth defects and miscarriage in clinically recognized pregnancies is 2% – 4% and 15% – 20%, respectively.

8.2 Lactation

Risk Summary

There is no information regarding the presence of mosunetuzumab-axgb in human milk, the effect on the breastfed child, or milk production. Because human IgG is present in human milk, and there is potential for mosunetuzumab-axgb absorption leading to B-cell depletion, advise women not to breastfeed during treatment with LUNSUMIO and for 3 months after the last dose.

8.3 Females and Males of Reproductive Potential

LUNSUMIO may cause fetal harm when administered to a pregnant woman [see Use in Specific Populations (8.1)].

Pregnancy Testing

Verify pregnancy status in females of reproductive potential prior to initiating LUNSUMIO.

Contraception

Females

Advise females of reproductive potential to use effective contraception during treatment with LUNSUMIO and for 3 months after the last dose.

8.4 Pediatric Use

The safety and efficacy of LUNSUMIO have not been established in pediatric patients.

8.5 Geriatric Use

Among the 90 patients with relapsed or refractory follicular lymphoma treated with LUNSUMIO, 33% were 65 years of age or older, and 8% were 75 years of age or older. There is an insufficient number of patients 65 years of age or older and 75 years of age or older to assess whether there are differences in safety or effectiveness in patients 65 years of age and older compared to younger adult patients.

11 DESCRIPTION

Mosunetuzumab-axgb is a bispecific CD20-directed CD3 T-cell engager. It is a humanized monoclonal anti-CD20xCD3 T-cell-dependent bispecific antibody of the immunoglobulin G1 (IgG1) isotype. Mosunetuzumab-axgb is produced in Chinese Hamster Ovary (CHO) cells by recombinant DNA technology. The approximate molecular weight is 146 kDa.

LUNSUMIO (mosunetuzumab-axgb) injection is a sterile, preservative-free, colorless solution for intravenous use.

Each single-dose vial contains a 1 mL solution of mosunetuzumab-axgb (1 mg), acetic acid (0.4 mg), histidine (1.6 mg), methionine (1.5 mg), polysorbate 20 (0.6 mg), sucrose (82.1 mg), and Water for Injection, USP. The pH is 5.8.

Each single-dose vial contains a 30 mL solution of mosunetuzumab-axgb (30 mg), acetic acid (12.8 mg), histidine (46.6 mg), methionine (44.8 mg), polysorbate 20 (18 mg), sucrose (2,462.4 mg), and Water for Injection, USP. The pH is 5.8.

12 CLINICAL PHARMACOLOGY

12.1 Mechanism of Action

Mosunetuzumab-axgb is a T-cell engaging bispecific antibody that binds to the CD3 receptor expressed on the surface of T-cells and CD20 expressed on the surface of lymphoma cells and some healthy B-lineage cells.

In vitro, mosunetuzumab-axgb activated T-cells, caused the release of proinflammatory cytokines, and induced lysis of B-cells.

12.2 Pharmacodynamics

After intravenous administration of the recommended dosage of LUNSUMIO, peripheral B-cell counts decreased to undetectable levels (< 5 cells/microliter) in most patients (95%) by Cycle 2 Day 1 and the depletion was sustained at later cycles including at Cycle 4 and Cycle 8.

LUNSUMIO caused hypogammaglobulinemia (defined as IgG levels < 500 mg/dL). Among 67 patients with baseline IgG levels ≥ 500 mg/dL, 40% had their IgG level decreased to < 500 mg/dL after administration of the recommended dosage of LUNSUMIO.

Plasma concentrations of cytokines (IL-2, IL-6, IL-10, TNF-α, and IFN-γ) were measured, and transient elevation of cytokines were observed at doses of 0.4 mg and above. After administration of the recommended dosage of LUNSUMIO, the highest elevation of cytokines was observed within 24 hours after the first dose on Cycle 1 Day 1 and after the first 60 mg dose on Cycle 1 Day 15. The elevated cytokine levels generally returned to baseline prior to the next infusion on Cycle 1 Day 8 and on Cycle 2 Day 1.

12.3 Pharmacokinetics

Mosunetuzumab-axgb PK exposure increased proportionally over a dose range from 0.2 mg to 60 mg (0.007 to 2 times the recommended treatment dosage). PK exposures for the recommended dosage of LUNSUMIO are summarized in Table 10 and Figure 1.

Table 10. Exposure Parameters of Mosunetuzumab-axgb Intravenous Infusion
 | AUC (day∙μg/mL) [Values are geometric mean with geometric CV%.] | Cmax (μg/mL) | Ctrough (μg/mL)
Cycle 1 (0 ‒ 21 days) | 35.2 (36.6) | 11.1 (36.7) | 2.6 (54.0)
Cycle 2 (21 ‒ 42 days) | 90.3 (48.5) | 13.6 (37.7) | 2.0 (83.1)
Cycle 3 (42 – 63 days) | 59.0 (48.9) | 7.6 (40.1) | 1.4 (75.6)
Steady state [Steady state values are approximated at Cycle 4 (63 ‒ 84 days).] | 52.9 (40.7) | 7.0 (37.9) | 1.3 (59.9)
All values reported are model-predicted exposure metrics.

Figure 1. Model-Predicted Mosunetuzumab-axgb Intravenous Infusion Concentration Time Profile

Pharmacokinetic parameters (Table 11) were evaluated at the recommended dosage and are presented as geometric mean (CV%) unless otherwise specified.

Table 11. Mosunetuzumab-axgb Pharmacokinetic Parameters in Patients with Relapsed or Refractory Follicular Lymphoma
Parameter | LUNSUMIO via Intravenous Infusion
Tmax median (range), hours [Steady-state.] | 4.0 (4.0 – 4.0) [Tmax is at the end of intravenous infusion.]
Volume of distributiona (L) | 5.5 (31%)
Half-lifea (days) | 16.1 (17%)
Systemic clearance (L/day) | 1.1 (63%) at baseline 0.58 (18%) at steady state
Tmax = time to peak concentration

Specific Populations

There were no clinically significant differences in the pharmacokinetics of mosunetuzumab-axgb based on age (19 to 96 years), sex, race (Asian and Non-Asian), ethnicity (Hispanic/Latino and not Hispanic/Latino), mild or moderate renal impairment (estimated creatinine clearance [CrCL] by Cockcroft-Gault formula: 30 to 89 mL/min), or mild hepatic impairment (total bilirubin less than or equal to upper limit of normal [ULN] with AST greater than ULN or total bilirubin greater than 1 to 1.5 times ULN with any AST). The effects of severe renal impairment (CrCL 15 to 29 mL/min) or moderate to severe hepatic impairment (total bilirubin greater than 1.5 times ULN with any AST) on the pharmacokinetics of mosunetuzumab-axgb are unknown.

Drug Interaction Studies

No clinical studies evaluating the drug interaction potential of mosunetuzumab-axgb have been conducted.

12.6 Immunogenicity

The observed incidence of anti-drug antibodies is highly dependent on the sensitivity and specificity of the assay. Differences in assay methods preclude meaningful comparisons of the incidence of anti-drug antibodies in the study described below with the incidence of anti-drug antibodies in other studies, including those of mosunetuzumab-axgb.

During treatment in Study GO29781 (up to 12 months) [see Clinical Studies (14)], using an enzyme-linked immunosorbent assay (ELISA), no patients (N = 418) treated with LUNSUMIO developed anti-mosunetuzumab-axgb antibodies. Based on these data, the clinical relevance of anti-mosunetuzumab-axgb antibodies could not be assessed.

13 NONCLINICAL TOXICOLOGY

13.1 Carcinogenesis, Mutagenesis, Impairment of Fertility

No carcinogenicity or genotoxicity studies have been conducted with mosunetuzumab-axgb.

No dedicated studies have been conducted to evaluate the effects of mosunetuzumab-axgb on fertility. No adverse effects on either male or female reproductive organs were identified in a 26-week repeat dose chronic toxicity study in sexually mature cynomolgus monkeys.

14 CLINICAL STUDIES

The efficacy of LUNSUMIO was evaluated in an open-label, multicenter, multi-cohort study (GO29781, NCT02500407) in patients with relapsed or refractory follicular lymphoma (FL) who had received at least two prior therapies, including an anti-CD20 monoclonal antibody and an alkylating agent. The study excluded patients with active infections, history of autoimmune disease, prior allogeneic transplant, or any history of CNS lymphoma or CNS disorders.

Patients received step-up doses of 1 mg on Cycle 1 Day 1 and 2 mg on Cycle 1 Day 8, followed by 60 mg on Cycle 1 Day 15, and 60 mg on Cycle 2 Day 1, then 30 mg via intravenous infusion every 3 weeks in subsequent cycles. A treatment cycle was 21 days. LUNSUMIO was administered for 8 cycles unless patients experienced progressive disease or unacceptable toxicity. After 8 cycles, patients with a complete response discontinued therapy; patients with a partial response or stable disease continued treatment up to 17 cycles, unless patients experienced progressive disease or unacceptable toxicity.

Among the 90 patients with relapsed or refractory FL, the median age was 60 years (range: 29 to 90 years), 33% were 65 years of age or older, 61% were male, 82% were White, 9% were Asian, 4% were Black or African American, and 8% were Hispanic or Latino. A total of 77% of patients had Stage III-IV disease, 34% had bulky disease, and all patients had an Eastern Cooperative Oncology Group (ECOG) performance status of 0 or 1. The median number of prior therapies was 3 (range: 2 to 10), with 38% receiving 2 prior therapies, 31% receiving 3 prior therapies, and 31% receiving more than 3 prior therapies.

Seventy-nine percent of patients were refractory to prior anti-CD20 monoclonal antibody therapy, 53% were refractory to both anti-CD20 monoclonal antibody and alkylator therapy, 9% received prior rituximab plus lenalidomide therapy, 21% received prior autologous stem cell transplant, and 3% received prior CAR-T therapy. Fifty-two percent of patients had progression of disease within 24 months of first systemic therapy.

Efficacy was established on the basis of objective response rate (ORR) and duration of response (DOR) as assessed by an independent review facility according to standard criteria for NHL (Cheson 2007). The median follow-up for DOR was 14.9 months. The efficacy results are summarized in Table 12.

Table 12. Efficacy Results in Patients with Relapsed or Refractory FL Who Received LUNSUMIO Intravenous Infusion
Response | LUNSUMIO N = 90
Objective response rate (ORR), n (%) | 72 (80)
(95% CI) | (70, 88)
Complete response (CR), n (%) | 54 (60)
(95% CI) | (49, 70)
Partial response (PR), n (%) | 18 (20)
(95% CI) | (12, 30)
Duration of response (DOR) | N = 72
Median DOR [DOR is defined as the time from the initial occurrence of a documented PR or CR until the patient experienced an event (documented disease progression or death due to any cause).] , [Kaplan-Meier estimate.] , months (95% CI) | 22.8 (10, NR)
Rate of continued response
At 12 months, % | 62
(95% CI) | (50, 74)
At 18 months, % | 57
(95% CI) | (44, 70)
CI = confidence interval; NR = not reached

The median time to first response was 1.4 months (range: 1.1 to 8.9).

16 HOW SUPPLIED/STORAGE AND HANDLING

LUNSUMIO (mosunetuzumab-axgb) injection is a sterile, colorless, preservative-free solution for intravenous infusion supplied as follows:

- One 1 mg/mL single-dose vial in a carton (NDC 50242-159-01)
- One 30 mg/30 mL (1 mg/mL) single-dose vial in a carton (NDC 50242-142-01).

STORAGE AND HANDLING

Store refrigerated at 2°C to 8°C (36°F to 46°F) in the original carton to protect from light.

Do not freeze. Do not shake.

17 PATIENT COUNSELING INFORMATION

Advise the patient to read the FDA-approved patient labeling (Medication Guide).

Cytokine Release Syndrome (CRS) – Discuss the signs and symptoms associated with CRS, including fever, chills, hypotension, tachycardia, hypoxia, and headache. Counsel patients to seek immediate medical attention should signs or symptoms of CRS occur at any time. Advise patients who experience symptoms that impair consciousness not to drive and refrain from operating heavy or potentially dangerous machinery until events resolve [see Warnings and Precautions (5.1)].

Neurologic Toxicity, including ICANS – Discuss the signs and symptoms associated with neurologic toxicity, including ICANS, headache, peripheral neuropathy, dizziness, or mental status changes. Advise patients to immediately contact their healthcare provider if they experience any signs or symptoms of neurologic toxicity. Advise patients who experience neurologic toxicity that impairs consciousness to refrain from driving or operating heavy or potentially dangerous machinery until neurologic toxicity resolves [see Warnings and Precautions (5.2)].

Infections – Discuss the signs or symptoms associated with infection [see Warnings and Precautions (5.3)].

Hemophagocytic Lymphohistiocytosis (HLH) – Discuss the signs and symptoms associated with HLH, including fever, coagulopathy, cytopenias, and splenomegaly [see Warnings and Precautions (5.4)].

Cytopenias – Discuss the signs and symptoms associated with cytopenias, including neutropenia and febrile neutropenia, anemia, and thrombocytopenia [see Warnings and Precautions (5.5)].

Tumor Flare – Inform patients of the potential risk of tumor flare reaction and to report any signs and symptoms associated with this event to their healthcare provider for evaluation [see Warnings and Precautions (5.6)].

Embryo-Fetal Toxicity – Advise pregnant women of the potential risk to a fetus. Advise females of reproductive potential to inform their healthcare provider if they are pregnant or become pregnant [see Use in Specific Populations (8.1)]. Advise females of reproductive potential to use effective contraception during treatment with LUNSUMIO and for 3 months after the last dose [see Use in Specific Populations (8.3)].

Lactation – Advise women not to breastfeed during treatment with LUNSUMIO and for 3 months after the last dose [see Use in Specific Populations (8.2)].

Manufactured by:
Genentech, Inc.
A Member of the Roche Group
1 DNA Way
South San Francisco, CA 94080-4990

LUNSUMIO is a registered trademark of Genentech, Inc.
©2025 Genentech, Inc.

U.S. License No.: 1048

MEDICATION GUIDE
LUNSUMIO® (lun-SUM-mee-oh)
(mosunetuzumab-axgb)
injection, for intravenous infusion

What is the most important information I should know about LUNSUMIO?
LUNSUMIO may cause Cytokine Release Syndrome (CRS), a serious side effect that is common during treatment with LUNSUMIO, and can also be severe or life-threatening.

Get medical help right away if you develop any signs or symptoms of CRS at any time, including:

- fever of 100.4°F (38°C) or higher
- chills
- low blood pressure
- fast or irregular heartbeat
- tiredness or weakness
- difficulty breathing

- headache
- confusion
- feeling anxious
- dizziness or light-headedness
- nausea
- vomiting

Due to the risk of CRS, you will receive LUNSUMIO on a "step-up dosing schedule".

- The step-up dosing schedule is when you receive smaller "step-up" doses of LUNSUMIO on Day 1 and Day 8 of your first cycle of treatment.
- You will receive a higher dose of LUNSUMIO on Day 15 of your first cycle of treatment.
- If your dose of LUNSUMIO is delayed for any reason, you may need to repeat the "step-up dosing schedule."
- Before each dose in Cycle 1 and Cycle 2, you will receive medicines to help reduce your risk of CRS.
- See "How will I receive LUNSUMIO?" for more information about how you will receive LUNSUMIO.

Your healthcare provider will check you for CRS during treatment with LUNSUMIO and may treat you in a hospital if you develop signs and symptoms of CRS. Your healthcare provider may temporarily stop or completely stop your treatment with LUNSUMIO if you have severe side effects.
See "What are the possible side effects of LUNSUMIO?" for more information about side effects.

What is LUNSUMIO?
LUNSUMIO is a prescription medicine used to treat adults with follicular lymphoma whose cancer has come back or did not respond to previous treatment, and who have already received two or more treatments for their cancer.
It is not known if LUNSUMIO is safe and effective in children.

Before receiving LUNSUMIO, tell your healthcare provider about all of your medical conditions, including if you:

- have ever had an infusion reaction after receiving LUNSUMIO.
- have an infection or have had an infection in the past which lasted a long time or keeps coming back.
- have or had Epstein-Barr Virus.
- are pregnant or plan to become pregnant. LUNSUMIO may harm your unborn baby. Tell your healthcare provider right away if you become pregnant or think you may be pregnant during treatment with LUNSUMIO.
  Females who are able to become pregnant:
  - your healthcare provider should do a pregnancy test before you start treatment with LUNSUMIO.
  - you should use an effective method of birth control (contraception) during your treatment and for 3 months after the last dose of LUNSUMIO.
- are breastfeeding or plan to breastfeed. It is not known if LUNSUMIO passes into your breast milk. Do not breastfeed during treatment and for 3 months after the last dose of LUNSUMIO.

Tell your healthcare provider about all the medicines you take, including prescription and over-the-counter medicines, vitamins, and herbal supplements.

How will I receive LUNSUMIO?

- LUNSUMIO will be given to you by your healthcare provider by infusion through a needle placed in a vein (intravenous infusion).
- After you complete the weekly "step-up dosing schedule" in Cycle 1, LUNSUMIO is given every 21 days.
- After Cycle 1 and Cycle 2, your healthcare provider will decide if you need to continue to take other medicines to help reduce side effects from LUNSUMIO during future cycles.
- Your healthcare provider will decide how many treatment cycles you will receive of LUNSUMIO.

See "What is the most important information I should know about LUNSUMIO?" for more information about how you will receive LUNSUMIO.

What should I avoid while receiving LUNSUMIO?
Do not drive, operate heavy machinery, or do other dangerous activities if you develop dizziness, confusion, tremors, sleepiness, or any other symptoms that impair consciousness until your signs and symptoms go away. These may be signs and symptoms of CRS or neurologic problems.
See "What is the most important information I should know about LUNSUMIO?" and "What are the possible side effects of LUNSUMIO?" for more information about signs and symptoms of CRS and neurologic problems.

What are the possible side effects of LUNSUMIO?
LUNSUMIO may cause serious side effects, including:
See "What is the most important information I should know about LUNSUMIO?"

- neurologic problems. LUNSUMIO can cause serious and life-threatening neurologic problems. Your healthcare provider will check you for neurologic problems during treatment with LUNSUMIO. Your healthcare provider may also refer you to a healthcare provider who specializes in neurologic problems. Tell your healthcare provider right away if you develop any signs or symptoms of neurologic problems during or after treatment with LUNSUMIO, including:

- headache
- numbness and tingling of the arms, legs, hands, or feet
- dizziness
- confusion and disorientation
- difficulty paying attention or understanding things
- forgetting things or forgetting who or where you are
- trouble speaking, reading, or writing

- sleepiness or trouble sleeping
- tremors
- loss of consciousness
- seizures
- muscle problems or muscle weakness
- loss of balance or trouble walking
- tiredness

- serious infections. LUNSUMIO can cause serious infections that may lead to death. Your healthcare provider will check you for signs and symptoms of infection before and during treatment. Tell your healthcare provider right away if you develop any signs or symptoms of infection during treatment with LUNSUMIO, including:

- fever of 100.4°F (38°C) or higher
- cough
- chest pain
- tiredness
- shortness of breath

- painful rash
- sore throat
- pain during urination
- feeling weak or generally unwell

- hemophagocytic lymphohistiocytosis (HLH). LUNSUMIO can cause overactivity of the immune system, a condition called hemophagocytic lymphohistiocytosis (HLH). HLH can be life-threatening and has led to death in people treated with LUNSUMIO. Your healthcare provider will check you for HLH especially if your CRS lasts longer than expected. Signs and symptoms of HLH include:

- fever
- enlarged spleen
- easy bruising

- low blood cell counts
- liver problems

- low blood cell counts. Low blood cell counts are common during treatment with LUNSUMIO and can also be serious or severe.
  Your healthcare provider will check your blood cell counts during treatment with LUNSUMIO. LUNSUMIO can cause the following low blood cell counts:
  - low white blood cell counts (neutropenia). Low white blood cells can increase your risk for infection.
  - low red blood cell counts (anemia). Low red blood cells can cause tiredness and shortness of breath.
  - low platelet counts (thrombocytopenia). Low platelet counts can cause bruising or bleeding problems.
- growth in your tumor or worsening of tumor related problems (tumor flare). LUNSUMIO can cause serious or severe worsening of your tumor.
  Tell your healthcare provider if you develop any of these signs or symptoms of tumor flare during your treatment with LUNSUMIO:

- chest pain
- cough
- trouble breathing

- tender or swollen lymph nodes
- pain or swelling at the site of the tumor

Your healthcare provider may temporarily stop or permanently stop treatment with LUNSUMIO if you develop severe side effects.
The most common side effects of LUNSUMIO include:

- cytokine release syndrome
- tiredness
- rash
- headache
- fever

- muscle pain
- cough
- itching
- numbness, tingling, or pain in the hands or feet (nerve damage)

The most common severe abnormal blood test results with LUNSUMIO include: decreased blood cell counts, decreased phosphate, increased glucose, and increased uric acid levels.
These are not all the possible side effects of LUNSUMIO.
Call your doctor for medical advice about side effects. You may report side effects to FDA at 1-800-FDA-1088.

General information about the safe and effective use of LUNSUMIO.
Medicines are sometimes prescribed for purposes other than those listed in a Medication Guide. You can ask your pharmacist or healthcare provider for information about LUNSUMIO that is written for health professionals.

What are the ingredients in LUNSUMIO?
Active ingredient: mosunetuzumab-axgb
Inactive ingredients: acetic acid, histidine, methionine, polysorbate 20, sucrose, and Water for Injection
Manufactured by: Genentech, Inc., A Member of the Roche Group, 1 DNA Way, South San Francisco, CA 94080-4990
U.S. License No.: 1048
LUNSUMIO is a registered trademark of Genentech, Inc.
For more information, call 1-844-832-3687 or go to www.LUNSUMIO.com.

This Medication Guide has been approved by the U.S. Food and Drug Administration.

Revised: Dec 2025

PRINCIPAL DISPLAY PANEL - 30 mg/30 mL Vial Carton

NDC 50242-142-01
Lunsumio®
(mosunetuzumab-axgb)
Injection

30 mg/30 mL
(1 mg/mL)

For Intravenous Infusion Only.

Single-Dose Vial.

Discard Unused Portion.

ATTENTION: Dispense the enclosed
Medication Guide to each patient.

1 vial

Rx only
Genentech

11042398

PRINCIPAL DISPLAY PANEL - 1 mg/mL Vial Carton

NDC 50242-159-01
Lunsumio®
(mosunetuzumab-axgb)
Injection

1 mg/mL

For Intravenous Infusion Only.

Single-Dose Vial.

Discard Unused Portion.

ATTENTION: Dispense the enclosed
Medication Guide to each patient.

1 vial

Rx only
Genentech

11042421